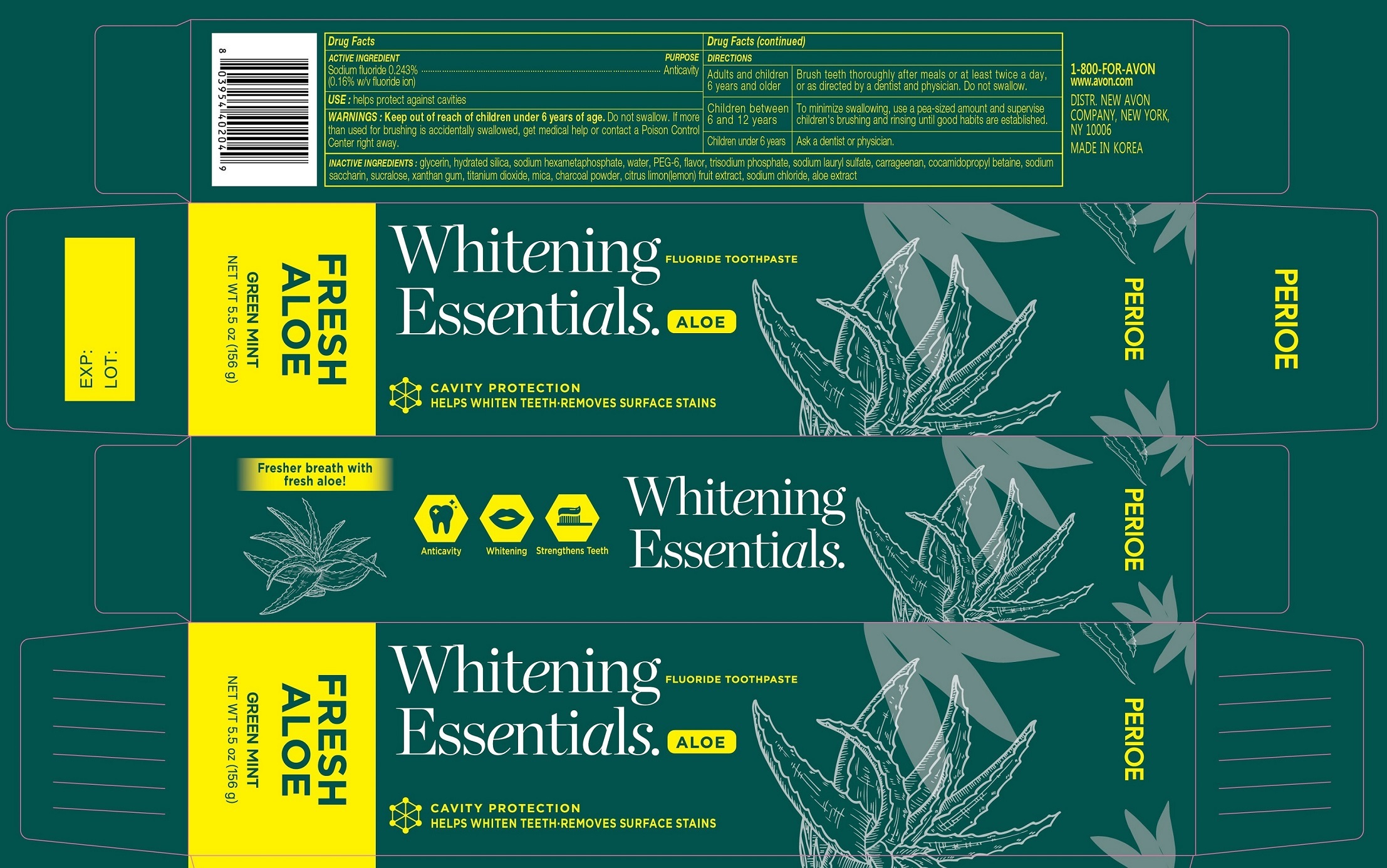 DRUG LABEL: PERIOE Whitening Essentials
NDC: 43136-802 | Form: PASTE, DENTIFRICE
Manufacturer: Tai Guk Pharm. Co., Ltd.
Category: otc | Type: HUMAN OTC DRUG LABEL
Date: 20250101

ACTIVE INGREDIENTS: SODIUM FLUORIDE 1.6 mg/1 g
INACTIVE INGREDIENTS: HEXASODIUM HEXAMETAPHOSPHATE; CARRAGEENAN; GLYCERIN; WATER; POLYETHYLENE GLYCOL 300; SODIUM PHOSPHATE, TRIBASIC, ANHYDROUS; SODIUM LAURYL SULFATE; COCAMIDOPROPYL BETAINE; SACCHARIN SODIUM; SUCRALOSE; TITANIUM DIOXIDE; CITRUS LIMON FRUIT OIL; SODIUM CHLORIDE; HYDRATED SILICA; XANTHAN GUM; MICA; ACTIVATED CHARCOAL; SILICON DIOXIDE; ALOE

PERIOE Whitening Essentials Fresh Aloe Green Mint

Drug Facts

Active Ingredient

Sodium fluoride 0.243% (0.16% w/v fluoride ion)

Purpose

Anticavity

Use

helps protect against cavities

Warnings

Keep out of reach of children under 6 years of age.Do not swallow. If more than used for brushing is accidentally swallowed, get medical help or contact a Poison Control Center right away.

Directions

Adults and children 6 years and older | Brush teeth thoroughly after each means or at least twice a day, or as directed by a dentist and physician. Do not swallow.
Children between 6 and 12 years | To minimize swallowing, use a pea-sized amount and supervise children's brushing and rinsing until good habits are established.
Children under 6 years | Ask a dentist or physician.

Inactive Ingredients

glycerin, hydrated silica, sodium hexametaphosphate, water, PEG-6, flavor, trisodium phosphate, sodium lauryl sulfate, carrageenan, cocamidopropyl betaine, sodium saccharin, sucralose, xanthan gum, titanium dioxide, mica, charcoal powder, citru limon(lemon) fruit extract, sodium chloride, aloe extract

QUESTIONS

1-800-FOR-AVON

www.avon.com

Principal Display Panel - 156 g Tube Carton

PERIOE

Whitening Essentials. ALOE

FLUORIDE TOOTHPASTE

CAVITY PROTECTION

HELPS WHITEN TEETH - REMOVES SURFACE STAINS

FRESH ALOE

GREEN MINT

NET WT 5.5 oz (156 g)